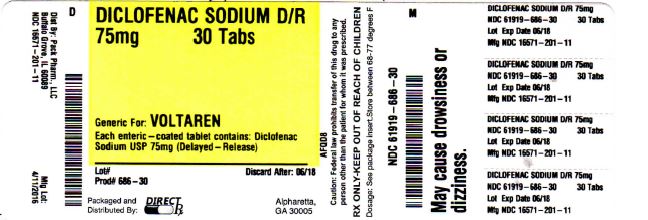 DRUG LABEL: DICLOFENAC SODIUM
NDC: 61919-686 | Form: TABLET, DELAYED RELEASE
Manufacturer: DIRECT RX
Category: prescription | Type: HUMAN PRESCRIPTION DRUG LABEL
Date: 20160413

ACTIVE INGREDIENTS: DICLOFENAC SODIUM 75 mg/1 1
INACTIVE INGREDIENTS: LACTOSE MONOHYDRATE; CELLULOSE, MICROCRYSTALLINE; POVIDONE, UNSPECIFIED; METHACRYLIC ACID - ETHYL ACRYLATE COPOLYMER (1:1) TYPE A; POLYETHYLENE GLYCOL, UNSPECIFIED; TITANIUM DIOXIDE; FERRIC OXIDE YELLOW; WATER; HYPROMELLOSES; FERRIC OXIDE RED; CROSCARMELLOSE SODIUM; TALC; MAGNESIUM STEARATE

DICLOFENAC SODIUM D\R 75mg 30 CAPS